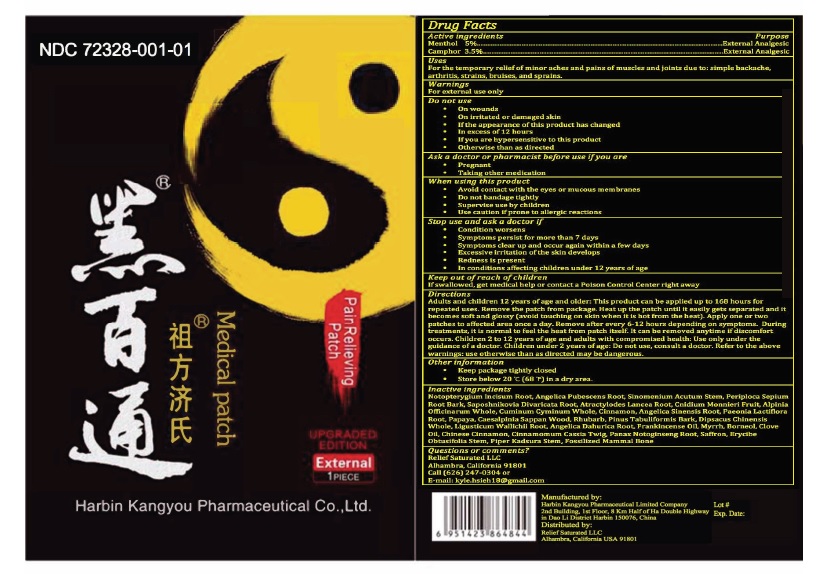 DRUG LABEL: Heibaitong Pain Relieving Patch
NDC: 72328-001 | Form: PATCH
Manufacturer: Harbin Kangyou Pharmaceutical Limited Company
Category: otc | Type: HUMAN OTC DRUG LABEL
Date: 20181211

ACTIVE INGREDIENTS: MENTHOL 5.0 g/100 g; CAMPHOR (SYNTHETIC) 3.5 g/100 g
INACTIVE INGREDIENTS: NOTOPTERYGIUM INCISUM ROOT; ANGELICA PUBESCENS ROOT; SINOMENIUM ACUTUM STEM; PERIPLOCA SEPIUM ROOT BARK; SAPOSHNIKOVIA DIVARICATA ROOT; ATRACTYLODES LANCEA ROOT; CNIDIUM MONNIERI FRUIT; ALPINIA OFFICINARUM WHOLE; CUMINUM CYMINUM WHOLE; CINNAMON; ANGELICA SINENSIS ROOT; PAEONIA LACTIFLORA ROOT; PAPAYA; CAESALPINIA SAPPAN WOOD; RHUBARB; PINUS TABULIFORMIS BARK; DIPSACUS CHINENSIS WHOLE; LIGUSTICUM WALLICHII ROOT; ANGELICA DAHURICA ROOT; FRANKINCENSE OIL; MYRRH; BORNEOL; CLOVE OIL; CHINESE CINNAMON; CINNAMOMUM CASSIA TWIG; PANAX NOTOGINSENG ROOT; SAFFRON; ERYCIBE OBTUSIFOLIA STEM; PIPER KADSURA STEM; MAMMAL BONE, FOSSILIZED

Harbin Kangyou Pharmaceutical Limited Company

ACTIVE INGREDIENTS

Menthol 5%

Camphor 3.5%

PURPOSE

Menthol External Analgesic

Camphor External Analgesic

USES

For the temporary relief of minor aches and pains of muscles and joints due to: simple backache, arthritis, strains, bruises, sprains.

Warnings

For External Use only.

Do not use

on wounds.
on irritated or damaged skin.
if the appearance of this product has changed.
in excess of 12 hours.
if you are hypersensitive to this product.
otherwise than as directed.

ASK A DOCTOR OR PHARMACIST BEFORE USE IF YOU ARE

pregnant.
taking other medications.

When using this product

avoid contact with the eye or mucous membranes.
do not bandage tightly.
supervise use by children.
use caution if prone to allergic reactions.

STOP USE AND ASK A DOCTOR IF

condition worsens.
symptoms persist for more than 7 days.
symptoms clear up and occur again within a few days.
excessive irritation of the skin develops.
redness is present.
in conditions affecting children under 12 years of age.

Keep out of reach of children.

If swallowed, get medical help or contact a Poison Control Center right away.

Directions

Adults and children 12 years of age and older: This product can be applied up to 168 hours of repeated uses. Remove the package from package. Heat up the patch until it easily gets separated and it becomes soft and glossy (avoid touching on skin when it is hot from the heat). Apply one or two patches to affected area once a day. Remove after every 6-12 hours depending on symptoms. During treatments, it is normal to feel the heat from patch itself. It can be removed anytime if discomfort occurs. Children 2 to 12 years of age and adults with compromised health: Use only under the guidance of a doctor. Children under 2 years of age: Do not use, consult a doctor. Refer to the above warnings: use otherwise than as directed may be dangerous.

Other Information

Keep container tightly closed.
Store below 20 ℃ (68 ℉) in a dry area.

Inactive Ingredients

NOTOPTERYGIUM INCISUM ROOT, ANGELICA PUBESCENS ROOT, SINOMENIUM ACUTUM STEM, PERIPLOCA SEPIUM ROOT BARK, SAPOSHNIKOVIA DIVARICATA ROOT, ATRACTYLODES LANCEA ROOT, CNIDIUM MONNIERI FRUIT, ALPINIA OFFICINARUM WHOLE, CUMINUM CYMINUM WHOLE, CINNAMON, ANGELICA SINENSIS ROOT, PAEONIA LACTIFLORA ROOT, PAPAYA, CAESALPINIA SAPPAN WOOD, RHUBARB, PINUS TABULIFORMIS BARK, DIPSACUS CHINENSIS WHOLE, LIGUSTICUM WALLICHII ROOT, ANGELICA DAHURICA ROOT, FRANKINCENSE OIL, MYRRH, BORNEOL, CLOVE OIL, CHINESE CINNAMON, CINNAMOMUM CASSIA TWIG, PANAX NOTOGINSENG ROOT, SAFFRON, ERYCIBE OBTUSIFOLIA STEM, PIPER KADSURA STEM, FOSSILIZED MAMMAL BONE

Questions or Comments?

Relief Saturated LLC
Alhambra, California 91801

Call (626) 247-0304 or
E-mail: kyle.hsieh18@gmail.com

Manufactured by Kangyou Pharmaceutical Limited Company 2nd Building, 1st Floor, 8 Km Half of Ha Double Highway in Dao Li District Harbin 150076, China

Distributed by

Relief Saturated LLC
Alhambra, California 91801 USA